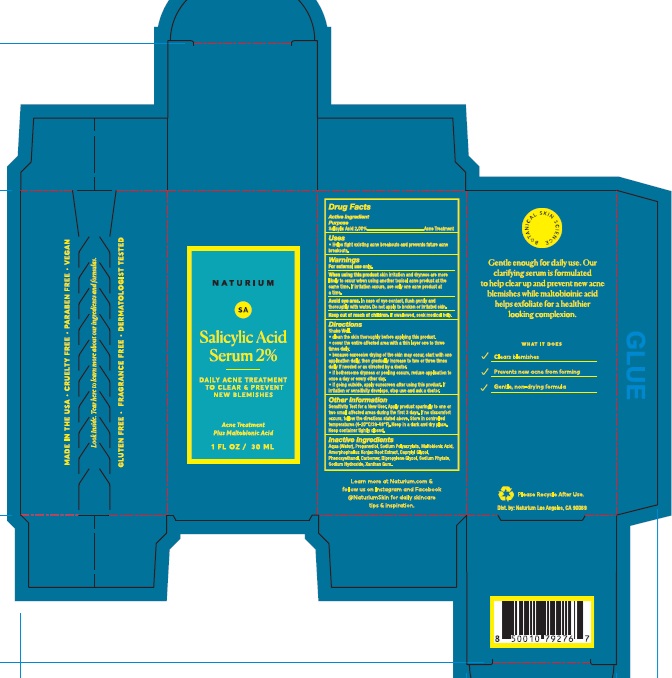 DRUG LABEL: Naturium Salicylic Acid Serum 2%
NDC: 76354-122 | Form: LIQUID
Manufacturer: e.l.f. Cosmetics, Inc
Category: otc | Type: HUMAN OTC DRUG LABEL
Date: 20251114

ACTIVE INGREDIENTS: SALICYLIC ACID 20 mg/1 mL
INACTIVE INGREDIENTS: MALTOBIONIC ACID; PHENOXYETHANOL; CARBOMER HOMOPOLYMER, UNSPECIFIED TYPE; SODIUM HYDROXIDE; XANTHAN GUM; DIPROPYLENE GLYCOL; WATER; SODIUM POLYACRYLATE (8000 MW); PROPANEDIOL; AMORPHOPHALLUS KONJAC ROOT; CAPRYLYL GLYCOL; PHYTATE SODIUM

Naturium Salicylic Acid Serum 2%

Active Ingredient

Salicylic Acid 2.00%

Purpose

Acne Treatment

Uses

- Helps fight existing acne breakouts and prevents future acne breakouts.

Warnings

For external use only.

When using this product

- skin irritation and dryness are more likely to occur when using another topical acne product at the same time. If irritation occurs, use only one acne product at a time.
- Avoid eye area. In case of eye contact, flush gently and thoroughly with water. Do not apply to broken or irritated skin.

Keep out of reach of children.

If swallowed, seek medical help.

Directions

Shake Well.

- clean the skin thoroughly before applying this product.
- cover the entire affected area with a thin layer one to three times daily.
- because excessive drying of the skin may occur, start with one application daily, then gradually increase to two or three times daily if needed or as directed by a doctor.
- if bothersome dryness or peeling occurs, reduce application to once a day or every other day.
- if going outside, apply sunscreen after using this product. If irritation or sensitivity develops, stop use and ask a doctor.

Other Information

Sensitivity Test for a New User. Apply product sparingly to one or two small affected areas during the first 3 days. If no discomfort occurs, follow the directions stated above. Store in controlled temperatures (4-20°C/39-68°F). Keep in a dark and dry place. Keep container tightly closed.

Inactive Ingredients

Aqua (Water), Propanediol, Sodium Polyacrylate, Maltobionic Acid, Amorphophallus Konjac Root Extract, Caprylyl Glycol, Phenoxyethanol, Carbomer, Dipropylene Glycol, Sodium Phytate, Sodium Hydroxide, Xanthan Gum.